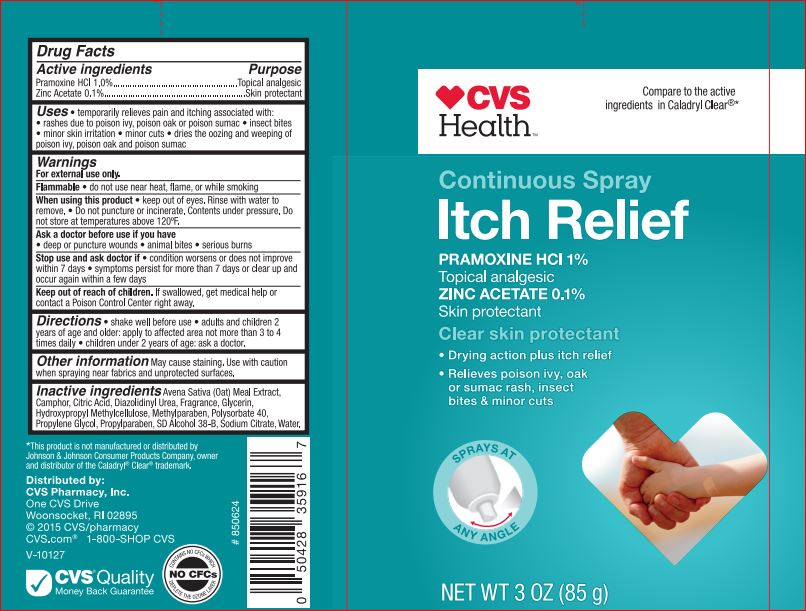 DRUG LABEL: Itch Relief Clear Skin Protectant
NDC: 59779-295 | Form: SPRAY
Manufacturer: CVS
Category: otc | Type: HUMAN OTC DRUG LABEL
Date: 20171130

ACTIVE INGREDIENTS: PRAMOXINE HYDROCHLORIDE 1 g/100 g; ZINC ACETATE .1 g/100 g
INACTIVE INGREDIENTS: ALCOHOL; OATMEAL; CAMPHOR (SYNTHETIC); CITRIC ACID MONOHYDRATE; DIAZOLIDINYL UREA; GLYCERIN; HYPROMELLOSE, UNSPECIFIED; METHYLPARABEN; POLYSORBATE 40; PROPYLENE GLYCOL; PROPYLPARABEN; SODIUM CITRATE; WATER

Drug Facts

Active ingredient

Pramoxine HCl 1%

Zinc Acetate 0.1%

Purpose

Itch Relief.

Uses

- Temporarily relieves pain and itching asociated with:
- rashes due to poison ivy, poison oak or poison sumac.
- insect bites.
- minor skin irritation.
- minor cuts.
- dries the oozing and weeping of poison ivy, poison oak and poison sumac.

Warnings

For external use only.

Flammable: Do not use near heat, flame, or while smoking.

When using this product

- keep out of eyes. Rinse with water to remove.
- Do not puncture or incinerate. Contents under pressure. Do no store at temperatures above 120F.

Stop use and ask a doctor if

- condition worsens or does not improve within 7 days.

- symptoms persist for more than 7 days or clear up and occur again with in a few days.

Keep out of reach of children

If swallowed, get medical help or contact a Poison Control Center right away.

Directions

- shake well before use.
- adults and children 2 years of age and older: apply to affected area not more than 3 to 4 times daily.
- children under 2 years of age: ask a doctor.

Inactive ingredients

SD Alcohol 38-B, Avena Sative (Oat Meal) Extract, Camphor, Citric Acid, Diazolidinyl Urea, Fragrance, Glycerin, Hypromellose, Methylparaben,Polysorbate 40, Propylene Glycol, Propylparaben, Sodium Citrate, Water.

PACKAGE LABEL

CVS Continuous Spray Itch Relief

Clear Skin Protectant

1% Pramoxine HCl

0.1% Zinc Acetate